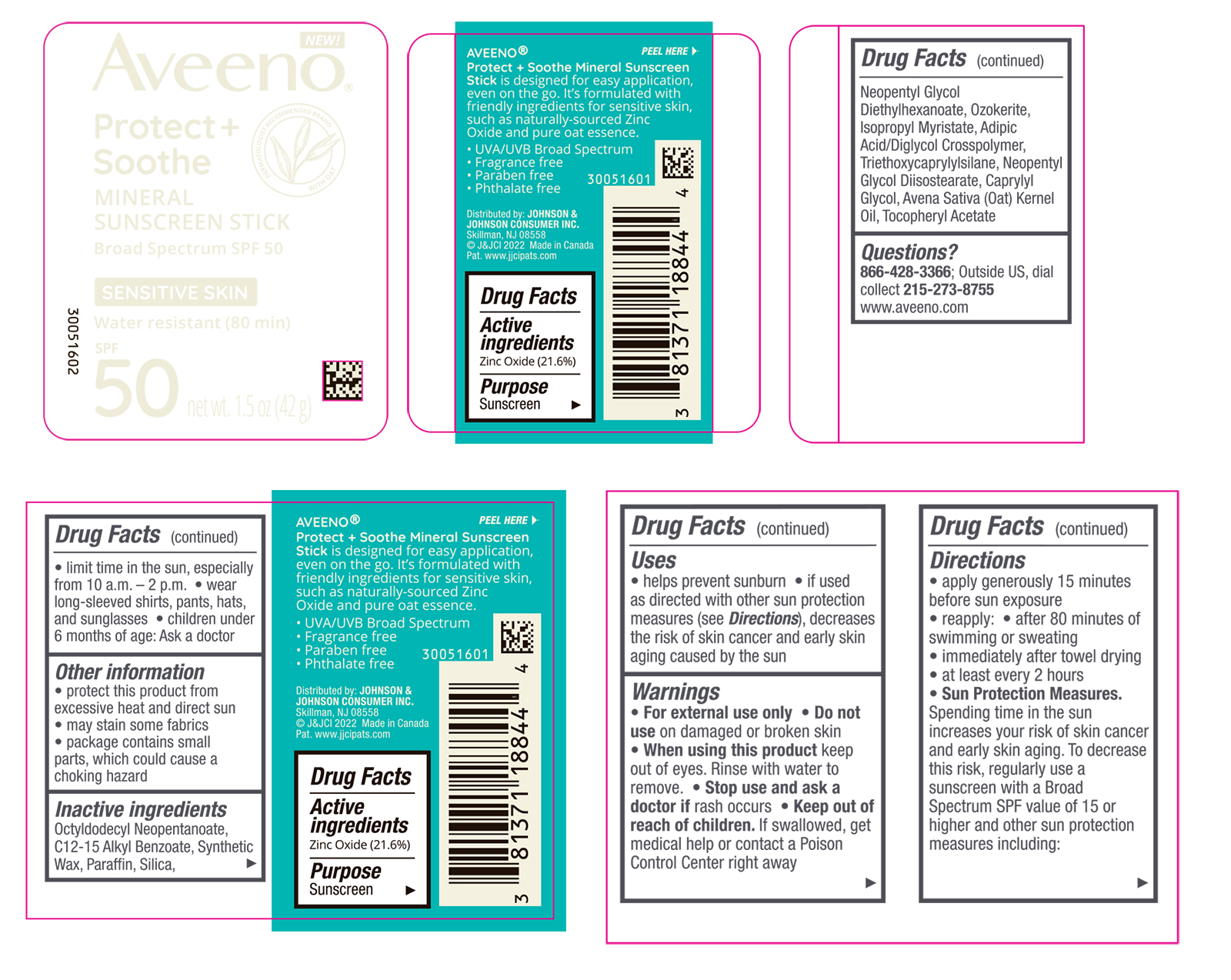 DRUG LABEL: Aveeno Protect Plus Soothe Mineral Sunscreen Broad Spectrum SPF 50
NDC: 69968-0780 | Form: STICK
Manufacturer: Kenvue Brands LLC
Category: otc | Type: HUMAN OTC DRUG LABEL
Date: 20250528

ACTIVE INGREDIENTS: ZINC OXIDE 216 mg/1 g
INACTIVE INGREDIENTS: OCTYLDODECYL NEOPENTANOATE; SILICON DIOXIDE; NEOPENTYL GLYCOL DIETHYLHEXANOATE; NEOPENTYL GLYCOL DIISOSTEARATE; CAPRYLYL GLYCOL; ALPHA-TOCOPHEROL ACETATE; ALKYL (C12-15) BENZOATE; PARAFFIN; ISOPROPYL MYRISTATE; ADIPIC ACID/DIGLYCOL CROSSPOLYMER (20000 MPA.S); TRIETHOXYCAPRYLYLSILANE; CERESIN; OAT KERNEL OIL

Aveeno Protect Plus Soothe Mineral Sunscreen Stick Broad Spectrum SPF 50

Drug Facts

ACTIVE INGREDIENT

Active ingredients | Purpose
Zinc Oxide (21.6%) | Sunscreen

Uses

- helps prevent sunburn
- if used as directed with other sun protection measures (see Directions), decreases the risk of skin cancer and early skin aging caused by the sun

Warnings

For external use only

Do not use on damaged or broken skin

When using this product

keep out of eyes. Rinse with water to remove.

Stop use and ask a doctor if rash occurs

Keep out of reach of children. If swallowed, get medical help or contact a Poison Control Center right away

Directions

- apply generously 15 minutes before sun exposure
- reapply:
  - after 80 minutes of swimming or sweating
  - immediately after towel drying
  - at least every 2 hours

- Sun Protection Measures. Spending time in the sun increases your risk of skin cancer and early skin aging. To decrease this risk, regularly use a sunscreen with a Broad-Spectrum SPF value of 15 or higher and other sun protection measures including:
- limit time in the sun, especially from 10 a.m. – 2 p.m.
- wear long-sleeved shirts, pants, hats, and sunglasses
- children under 6 months of age: Ask a doctor

Other information

- protect this product from excessive heat and direct sun
- may stain some fabrics
- package contains small parts, which could cause a choking hazard

Inactive ingredients

Octyldodecyl Neopentonate,C12-15 Alkyl Benzoate, Synthetic wax, Paraffin ,Silica, Neopentyl glycol, Diethylhexonate, Ozokerite, Isopropyl Myristate, Adipic Acid/Diglycol Crosspolymer ,Trihexocarpylsilane, Neopentyl Glycol Diisostearate, Caprylyl Glycol, Avena Sativa (Oat) Kernel Oil, Tocopheryl Acetate

Questions?

866-428-3366; Outside US, dial collect 215-273-8755 www.aveeno.com

Distributed by:
JOHNSON & JOHNSON CONSUMER INC.
Skillman, NJ 08558

PRINCIPAL DISPLAY PANEL - 42g Canister Label

New!

Aveeno®

Protect +

Soothe

MINERAL

SUNSCREEN STICK

Broad Spectrum SPF 50

SENSITIVE SKIN

Water resistant (80 min)

SPF

50

net wt.1.5 OZ

(42 g)